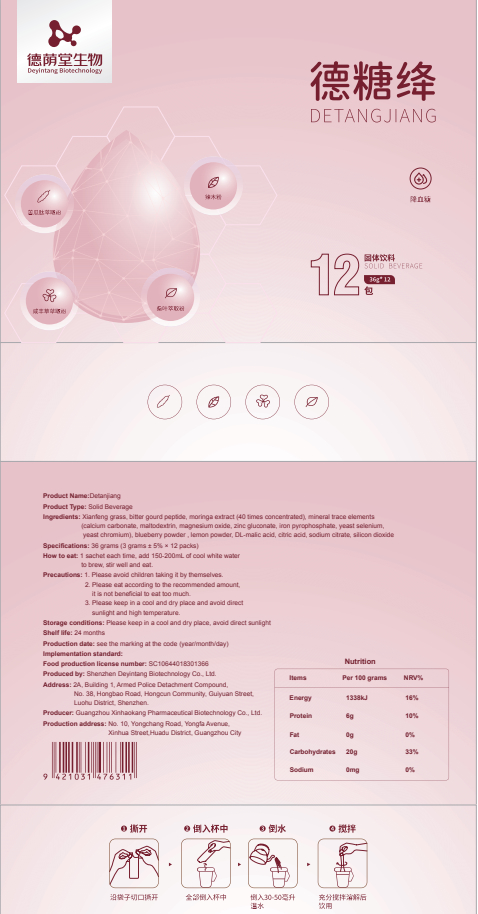 DRUG LABEL: Detangjiang
NDC: 82570-018 | Form: POWDER
Manufacturer: Shenzhen Deyintang Biotechnology Co., Ltd.
Category: otc | Type: HUMAN OTC DRUG LABEL
Date: 20220304

ACTIVE INGREDIENTS: COLLAGEN, SOLUBLE, FISH SKIN 10 g/100 g; SELENIUM 3 g/100 g; CHROMIUM 3 g/100 g; MAGNESIUM OXIDE 2 g/100 g; ZINC GLUCONATE 2 g/100 g; MORINGA OLEIFERA LEAF 40 g/100 g; BIDENS PILOSA LEAF 10 g/100 g; MOMORDICA CHARANTIA WHOLE 10 g/100 g
INACTIVE INGREDIENTS: BLUEBERRY; MALIC ACID; CITRIC ACID MONOHYDRATE; SILICON DIOXIDE; CRANBERRY

ACTIVE INGREDIENT

Xianfeng grass, bitter gourd peptide, moringa extract (40 times concentrated),magnesium oxide, zinc gluconate,yeast selenium,yeast, chromium,Fish Collagen Peptide

INACTIVE INGREDIENT

blueberry powder , lemon powder, DL -malic acid, citric acid, sodium citrate silicon dioxide

PURPOSE

health care

Please avoid children taking it by themselves.

DOSAGE AND ADMINISTRATION

1 sachet each time, add 150-200mL of cool white water to brew, stir well and eat.

INDICATIONS AND USAGE

Please eat according to the recommended amount,it is not beneficial to eat too much.

Storage conditions

Please keep in a cool and dry place, avoid direct sunlight

WARNINGS

1.Please avoid children taking it by themselves.
2. Please eat according to the recommended amount,it is not beneficial to eat too much.
3.Please keep in a cool and dry place and avoid directsunlight and high temperature.